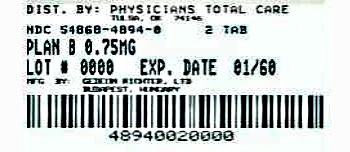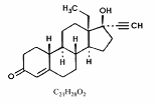 DRUG LABEL: Plan B
NDC: 54868-4894 | Form: TABLET
Manufacturer: Physicians Total Care, Inc.
Category: prescription | Type: HUMAN PRESCRIPTION DRUG LABEL
Date: 20120423

ACTIVE INGREDIENTS: LEVONORGESTREL 0.75 mg/1 1
INACTIVE INGREDIENTS: SILICON DIOXIDE; STARCH, CORN; GELATIN; LACTOSE MONOHYDRATE; MAGNESIUM STEARATE; STARCH, POTATO; TALC

HIGHLIGHTS OF PRESCRIBING INFORMATION

These highlights do not include all the information needed to use Plan B safely and effectively. See full prescribing information for Plan B.
Plan B (levonorgestrel) tablets, 0.75mg, for oral use
Initial U.S. Approval: 1982

1 INDICATIONS AND USAGE

Plan B is a progestin-only emergency contraceptive, indicated for prevention of pregnancy following unprotected intercourse or a known or suspected contraceptive failure. Plan B is available only by prescription for women younger than age 17 years, and available over the counter for women 17 years and older. Plan B is not intended for routine use as a contraceptive. (1)

2 DOSAGE AND ADMINISTRATION

The first tablet is taken orally as soon as possible within 72 hours after unprotected intercourse. The second tablet should be taken 12 hours after the first dose. Efficacy is better if Plan B is taken as soon as possible after unprotected intercourse. (2)

3 DOSAGE FORMS AND STRENGTHS

A total of two 0.75 mg tablets taken 12 hours apart as a single course of treatment (3)

4 CONTRAINDICATIONS

Known or suspected pregnancy. (4)

5 WARNINGS AND PRECAUTIONS

- Ectopic Pregnancy: Women who become pregnant or complain of lower abdominal pain after taking Plan B should be evaluated for ectopic pregnancy. (5.1)
- Plan B is not effective in terminating an existing pregnancy. (5.2)
- Effect on menses: Plan B may alter the next expected menses. If menses is delayed beyond 1 week, pregnancy should be considered. (5.3)
- STI/HIV: Plan B does not protect against STI/HIV. (5.4)

6 ADVERSE REACTIONS

The most common adverse reactions (≥ 10%) in the clinical trial included menstrual changes (26%), nausea (23%), abdominal pain (18%), fatigue (17%), headache (17%), dizziness (11%) and breast tenderness (11%). (6.1)

To report SUSPECTED ADVERSE REACTIONS, contact Barr Laboratories at 1-800-330-1271 or FDA at 1-800-FDA-1088 or www.fda.gov/medwatch

7 DRUG INTERACTIONS

Drugs or herbal products that induce certain enzymes, such as CYP3A4, may decrease the effectiveness of progestin-only pills. (7)

8 USE IN SPECIFIC POPULATIONS

- Nursing Mothers: Small amounts of progestin pass into the breast milk of nursing women taking progestin-only pills for long-term contraception, resulting in detectable steroid levels in infant plasma. (8.3)
- Plan B is not intended for use in pediatric (premenarcheal) (8.4) or postmenopausal women (8.5).
- Clinical trials demonstrated a higher pregnancy rate in the Chinese population. (8.6)

FULL PRESCRIBING INFORMATION

1 INDICATIONS AND USAGE

Plan B® is a progestin-only emergency contraceptive indicated for prevention of pregnancy following unprotected intercourse or a known or suspected contraceptive failure. To obtain optimal efficacy, the first tablet should be taken as soon as possible within 72 hours of intercourse. The second tablet should be taken 12 hours later.

Plan B is available only by prescription for women younger than age 17 years, and available over the counter for women 17 years and older.

Plan B is not indicated for routine use as a contraceptive.

2 DOSAGE AND ADMINISTRATION

Take one tablet of Plan B orally as soon as possible within 72 hours after unprotected intercourse or a known or suspected contraceptive failure. Efficacy is better if the tablet is taken as soon as possible after unprotected intercourse. The second tablet should be taken 12 hours after the first dose. Plan B can be used at any time during the menstrual cycle.

If vomiting occurs within two hours of taking either dose of medication, consideration should be given to repeating the dose.

3 DOSAGE FORMS AND STRENGTHS

Each Plan B tablet is supplied as a white, round tablet containing 0.75 mg of levonorgestrel and is marked with INOR on one side.

4 CONTRAINDICATIONS

Plan B is contraindicated for use in the case of known or suspected pregnancy.

5 WARNINGS AND PRECAUTIONS

5.1 Ectopic Pregnancy

Ectopic pregnancies account for approximately 2% of all reported pregnancies. Up to 10% of pregnancies reported in clinical studies of routine use of progestin-only contraceptives are ectopic.

A history of ectopic pregnancy is not a contraindication to use of this emergency contraceptive method. Healthcare providers, however, should consider the possibility of an ectopic pregnancy in women who become pregnant or complain of lower abdominal pain after taking Plan B. A follow-up physical or pelvic examination is recommended if there is any doubt concerning the general health or pregnancy status of any woman after taking Plan B.

5.2 Existing Pregnancy

Plan B is not effective in terminating an existing pregnancy.

5.3 Effects on Menses

Some women may experience spotting a few days after taking Plan B. Menstrual bleeding patterns are often irregular among women using progestin-only oral contraceptives and women using levonorgestrel for postcoital and emergency contraception.

If there is a delay in the onset of expected menses beyond 1 week, consider the possibility of pregnancy.

5.4 STI/HIV

Plan B does not protect against HIV infection (AIDS) or other sexually transmitted infections (STIs).

5.5 Physical Examination and Follow-up

A physical examination is not required prior to prescribing Plan B. A follow-up physical or pelvic examination is recommended if there is any doubt concerning the general health or pregnancy status of any woman after taking Plan B.

5.6 Fertility Following Discontinuation

A rapid return of fertility is likely following treatment with Plan B for emergency contraception; therefore, routine contraception should be continued or initiated as soon as possible following use of Plan B to ensure ongoing prevention of pregnancy.

6 ADVERSE REACTIONS

6.1 Clinical Trial Experience

Because clinical trials are conducted under widely varying conditions, adverse reaction rates observed in the clinical trials of a drug cannot be directly compared to rates in the clinical trials of another drug and may not reflect the rates observed in clinical practice.

A double-blind, controlled clinical trial in 1,955 evaluable women compared the efficacy and safety of Plan B (one 0.75 mg tablet of levonorgestrel taken within 72 hours of unprotected intercourse, and one tablet taken 12 hours later) to the Yuzpe regimen (two tablets each containing 0.25 mg levonorgestrel and 0.05 mg ethinyl estradiol, taken within 72 hours of intercourse, and two tablets taken 12 hours later).

The most common adverse events (>10%) in the clinical trial for women receiving Plan B included menstrual changes (26%), nausea (23%), abdominal pain (18%), fatigue (17%), headache (17%), dizziness (11%), and breast tenderness (11%). Table 1 lists those adverse events that were reported in ≥ 5% of Plan B users.

Table 1: Adverse Events in ≥ 5%of Women, by % Frequency
 | Plan B; Levonorgestrel; N=977 (%)
Nausea | 23.1
Abdominal Pain | 17.6
Fatigue | 16.9
Headache | 16.8
Heavier Menstrual Bleeding | 13.8
Lighter Menstrual Bleeding | 12.5
Dizziness | 11.2
Breast Tenderness | 10.7
Vomiting | 5.6
Diarrhea | 5.0

6.2 Postmarketing Experience

The following adverse reactions have been identified during post-approval use of Plan B. Because these reactions are reported voluntarily from a population of uncertain size, it is not always possible to reliably estimate their frequency or establish a causal relationship to drug exposure.

Gastrointestinal Disorders
Abdominal Pain, Nausea, Vomiting

General Disorders and Administration Site Conditions
Fatigue

Nervous System Disorders
Dizziness, Headache

Reproductive System and Breast Disorders
Dysmenorrhea, Irregular Menstruation, Oligomenorrhea, Pelvic Pain

7 DRUG INTERACTIONS

Drugs or herbal products that induce enzymes, including CYP3A4, that metabolize progestins may decrease the plasma concentrations of progestins, and may decrease the effectiveness of progestin-only pills. Some drugs or herbal products that may decrease the effectiveness of progestin-only pills include:

- barbiturates
- bosentan
- carbamazepine
- felbamate
- griseofulvin
- oxcarbazepine
- phenytoin
- rifampin
- St. John’s wort
- topiramate

Significant changes (increase or decrease) in the plasma levels of the progestin have been noted in some cases of co-administration with HIV protease inhibitors or with non-nucleoside reverse transcriptase inhibitors.

Consult the labeling of all concurrently used drugs to obtain further information about interactions with progestin-only pills or the potential for enzyme alterations.

8 USE IN SPECIFIC POPULATIONS

8.1 Pregnancy

Many studies have found no harmful effects on fetal development associated with long-term use of contraceptive doses of oral progestins. The few studies of infant growth and development that have been conducted with progestin-only pills have not demonstrated significant adverse effects.

8.3 Nursing Mothers

In general, no adverse effects of progestin-only pills have been found on breastfeeding performance or on the health, growth or development of the infant. However, isolated post-marketing cases of decreased milk production have been reported. Small amounts of progestins pass into the breast milk of nursing mothers taking progestin-only pills for long-term contraception, resulting in detectable steroid levels in infant plasma.

8.4 Pediatric Use

Safety and efficacy of progestin-only pills for long-term contraception have been established in women of reproductive age. Safety and efficacy are expected to be the same for postpubertal adolescents under the age of 16 and for users 16 years and older. Use of Plan B emergency contraception before menarche is not indicated.

8.5 Geriatric Use

This product is not intended for use in postmenopausal women.

8.6 Race

No formal studies have evaluated the effect of race. However, clinical trials demonstrated a higher pregnancy rate in Chinese women with both Plan B and the Yuzpe regimen (another form of emergency contraception). The reason for this apparent increase in the pregnancy rate with emergency contraceptives in Chinese women is unknown.

8.7 Hepatic Impairment

No formal studies were conducted to evaluate the effect of hepatic disease on the disposition of Plan B.

8.8 Renal Impairment

No formal studies were conducted to evaluate the effect of renal disease on the disposition of Plan B.

9 DRUG ABUSE AND DEPENDENCE

Levonorgestrel is not a controlled substance. There is no information about dependence associated with the use of Plan B.

10 OVERDOSAGE

There are no data on overdosage of Plan B, although the common adverse event of nausea and associated vomiting may be anticipated.

11 DESCRIPTION

Each Plan B tablet contains 0.75 mg of a single active steroid ingredient, levonorgestrel [18,19-Dinorpregn-4-en-20-yn-3-one-13-ethyl-17-hydroxy-, (17α)-(-)-], a totally synthetic progestogen. The inactive ingredients present are colloidal silicon dioxide, potato starch, gelatin, magnesium stearate, talc, corn starch, and lactose monohydrate. Levonorgestrel has a molecular weight of 312.45, and the following structural and molecular formulas:

12 CLINICAL PHARMACOLOGY

12.1 Mechanism of Action

Emergency contraceptive pills are not effective if a woman is already pregnant. Plan B is believed to act as an emergency contraceptive principally by preventing ovulation or fertilization (by altering tubal transport of sperm and/or ova). In addition, it may inhibit implantation (by altering the endometrium). It is not effective once the process of implantation has begun.

12.3 Pharmacokinetics

Absorption

No specific investigation of the absolute bioavailability of Plan B in humans has been conducted. However, literature indicates that levonorgestrel is rapidly and completely absorbed after oral administration (bioavailability about 100%) and is not subject to first pass metabolism.

After a single dose of Plan B (0.75 mg) administered to 16 women under fasting conditions, maximum serum concentrations of levonorgestrel were 14.1 + 7.7 ng/mL (mean + SD) at an average of 1.6 + 0.7 hours.

Table 2: Pharmacokinetic Parameter Values Following Single Dose Administration of Plan B (Levonorgestrel) Tablets 0.75 mg to Healthy Female Volunteers under Fasting Conditions
 | Mean (± SD)
 | Cmax (ng/mL) | Tmax (h) | CL (L/h) | Vd (L) | t½ (h) | AUCinf (ng/mL.h)
Levonorgestrel | 14.1 (7.7) | 1.6 (0.7) | 7.7 (2.7) | 260.0 | 24.4 (5.3) | 123.1 (50.1)
Cmax = maximum concentration
Tmax = time to maximum concentration
CL = clearance
Vd = volume of distribution
t1/2 = elimination half life
AUCinf = area under the drug concentration curve from time 0 to infinity

Effect of Food: The effect of food on the rate and the extent of levonorgestrel absorption following single oral administration of Plan B has not been evaluated.

Distribution

The apparent volume of distribution of levonorgestrel is reported to be approximately 1.8 L/kg. It is about 97.5 to 99% protein-bound, principally to sex hormone binding globulin (SHBG) and, to a lesser extent, serum albumin.

Metabolism

Following absorption, levonorgestrel is conjugated at the 17β-OH position to form sulfate conjugates and, to a lesser extent, glucuronide conjugates in plasma. Significant amounts of conjugated and unconjugated 3α, 5β-tetrahydrolevonorgestrel are also present in plasma, along with much smaller amounts of 3α, 5α-tetrahydrolevonorgestrel and 16βhydroxylevonorgestrel. Levonorgestrel and its phase I metabolites are excreted primarily as glucuronide conjugates. Metabolic clearance rates may differ among individuals by several-fold, and this may account in part for the wide variation observed in levonorgestrel concentrations among users.

Excretion

About 45% of levonorgestrel and its metabolites are excreted in the urine and about 32% are excreted in feces, mostly as glucuronide conjugates.

Specific Populations

Pediatric: This product is not intended for use in the pediatric (pre-menarcheal) population, and pharmacokinetic data are not available for this population.

Geriatric: This product is not intended for use in postmenopausal women and pharmacokinetic data are not available for this population.

Race: No formal studies have evaluated the effect of race on pharmacokinetics of Plan B. However, clinical trials demonstrated a higher pregnancy rate in Chinese women with both Plan B and the Yuzpe regimen (another form of emergency contraception). The reason for this apparent increase in the pregnancy rate with emergency contraceptives in Chinese women is unknown [see USE IN SPECIFIC POPULATIONS (8.6)].

Hepatic Impairment: No formal studies were conducted to evaluate the effect of hepatic disease on the disposition of Plan B.

Renal Impairment: No formal studies were conducted to evaluate the effect of renal disease on the disposition of Plan B.

Drug-Drug Interactions

No formal drug-drug interaction studies were conducted with Plan B [see DRUG INTERACTIONS (7)].

13 NONCLINICAL TOXICOLOGY

13.1 Carcinogenesis, Mutagenesis, Impairment of Fertility

Carcinogenicity: There is no evidence of increased risk of cancer with short-term use of progestins. There was no increase in tumorgenicity following administration of levonorgestrel to rats for 2 years at approximately 5 µg/day, to dogs for 7 years at up to 0.125 mg/kg/day, or to rhesus monkeys for 10 years at up to 250 µg/kg/day. In another 7 year dog study, administration of levonorgestrel at 0.5 mg/kg/day did increase the number of mammary adenomas in treated dogs compared to controls. There were no malignancies.

Genotoxicity: Levonorgestrel was not found to be mutagenic or genotoxic in the Ames Assay, in vitro mammalian culture assays utilizing mouse lymphoma cells and Chinese hamster ovary cells, and in an in vivo micronucleus assay in mice.

Fertility: There are no irreversible effects on fertility following cessation of exposures to levonorgestrel or progestins in general.

14 CLINICAL STUDIES

A double-blind, randomized, multinational controlled clinical trial in 1,955 evaluable women (mean age 27) compared the efficacy and safety of Plan B (one 0.75 mg tablet of levonorgestrel taken within 72 hours of unprotected intercourse, and one tablet taken 12 hours later) to the Yuzpe regimen (two tablets each containing 0.25 mg levonorgestrel and 0.05 mg ethinyl estradiol, taken within 72 hours of intercourse, and two additional tablets taken 12 hours later). After a single act of intercourse occurring anytime during the menstrual cycle, the expected pregnancy rate of 8% (with no contraceptive use) was reduced to approximately 1% with Plan B.

Emergency contraceptives are not as effective as routine hormonal contraception since their failure rate, while low based on a single use, would accumulate over time with repeated use [see INDICATIONS AND USAGE (1)].

At the time of expected menses, approximately 74% of women using Plan B had vaginal bleeding similar to their normal menses, 14% bled more than usual, and 12% bled less than usual. The majority of women (87%) had their next menstrual period at the expected time or within + 7 days, while 13% had a delay of more than 7 days beyond the anticipated onset of menses.

16 HOW SUPPLIED/STORAGE AND HANDLING

Plan B (levonorgestrel) tablets, 0.75 mg, are available for a single course of treatment in PVC/aluminum foil blister packages of two tablets each. The tablet is white, round and marked INOR on one side.

Available as: Unit-of-use NDC 54868-4894-0

Store Plan B tablets at controlled room temperature, 20° to 25°C (68° to 77°F); excursions permitted between 15° to 30°C (59° to 86°F) [see USP].

17 PATIENT COUNSELING INFORMATION

17.1 Information for Patients

- Take Plan B as soon as possible and not more than 72 hours after unprotected intercourse or a known or suspected contraceptive failure.
- If you vomit within two hours of taking either tablet, immediately contact your healthcare provider to discuss whether to take another tablet.
- Seek medical attention if you experience severe lower abdominal pain 3 to 5 weeks after taking Plan B, in order to be evaluated for an ectopic pregnancy.
- After taking Plan B, consider the possibility of pregnancy if your period is delayed more than one week beyond the date you expected your period.
- Do not use Plan B as routine contraception.
- Plan B is not effective in terminating an existing pregnancy.
- Plan B does not protect against HIV-infection (AIDS) and other sexually transmitted diseases/infections.
- For women younger than age 17 years, Plan B is available only by prescription.

Mfg. by Gedeon Richter, Ltd., Budapest, Hungary
for Duramed Pharmaceuticals, Inc.
Subsidiary of Barr Pharmaceuticals, Inc.
Pomona, New York 10970
Phone: 1-800-330-1271 Website: www.go2planb.com

BR- 0038/11001288

Revised July 2009

Additional barcode labeling by:
Physicians Total Care, Inc.
Tulsa, Oklahoma 74146

PRINCIPAL DISPLAY PANEL

NDC 54868-4894-0

Plan B®
(LEVONORGESTREL)
tablets 0.75 mg

Emergency Contraceptive

2 Levonorgestrel Tablets
0.75 mg each

The sooner you take the first tablet, the better Plan B® will work

Not for regular birth control.

Plan B® should be used only in emergencies.

1 Take first tablet as soon as possible, within 72 hours (3 days) after unprotected sex.

2 Take second tablet 12 hours after taking first tablet.

TIME REMINDER Write on line below, the time the first tablet is taken. Take second tablet 12 hours later

AM/PM (circle one)

Reduces the chance of pregnancy after unprotected sex (if a regular birth control method fails or after sex without birth control).

Rx only for women younger than age 17

Take the first tablet as soon as possible within 72 hours (3 days) after unprotected sex. The sooner you take the first tablet, the better Plan B® will work. Take the second tablet 12 hours later.

Drug Facts

Active ingredient (in each tablet) Purpose

Levonorgestrel 0.75mg......................Emergency contraceptive

Use reduces chance of pregnancy after unprotected sex (if a contraceptive failed or if you did not use birth control)

Warnings

Allergy alert: Do not use if you have ever had an allergic reaction to levonorgestrel

Sexually transmitted diseases (STDs) alert: This product does not protect against HIV/AIDS or other STDs

Do not use

- if you are already pregnant (because it will not work)
- for regular birth control

When using this product you may have

- menstrual changes
- nausea
- lower stomach (abdominal) pain
- tiredness
- headache
- dizziness
- breast pain
- vomiting

Keep out of reach of children. In case of overdose, get medical help or contact a Poison Control center right away.

Directions

- women 17 years of age or older:
- take the first tablet as soon as possible within
  72 hours (3 days) after unprotected sex. The sooner you
  take the first tablet, the better it will work.
- take the second tablet 12 hours after you take the first tablet
- if you vomit within 2 hours of taking the medication, call a
  healthcare professional to find out if you should repeat that dose
- prescription only for women younger than age 17. If you
  are younger than age 17, see a healthcare professional.

Other information

- before using this product read the enclosed consumer
  information leaflet for complete directions and information
- this product is not recommended for regular birth control. It
  does not work as well as most other birth control methods
  used correctly.
- this product works mainly by preventing ovulation (egg
  release). It may also prevent fertilization of a released egg
  (joining of sperm and egg) or attachment of a fertilized egg
  to the uterus (implantation).
- when used correctly every time you have sex, latex condoms
  greatly reduce, but do not eliminate, the risk of pregnancy and
  the risk of catching or spreading HIV, the virus that causes AIDS.
  See condom labeling for additional STD information.
- tablets are enclosed in a blister seal. Do not use if the blister
  seal is broken.
- store at 20-25°C (68-77°F)

Inactive ingredients

colloidal silicon dioxide, corn starch, gelatin, lactose monohydrate, magnesium stearate, potato starch, talc

Questions or comments?

For more information or to speak to a healthcare professional,
call 1-800-330-1271, 24 hours a day/7 days a week.

Visit our Web site at www.go2planb.com